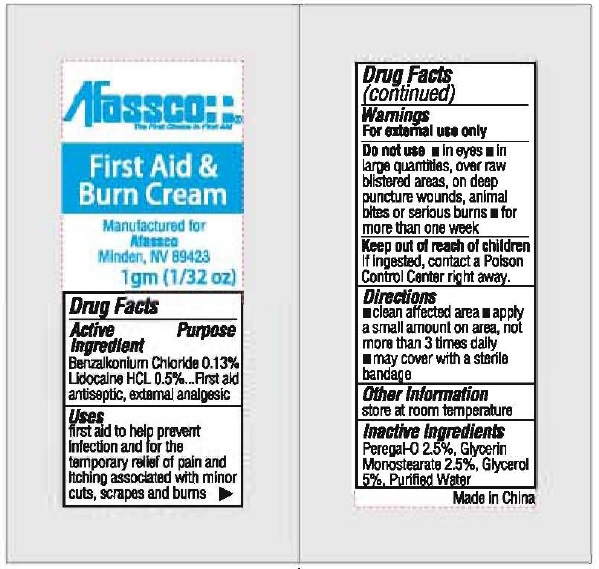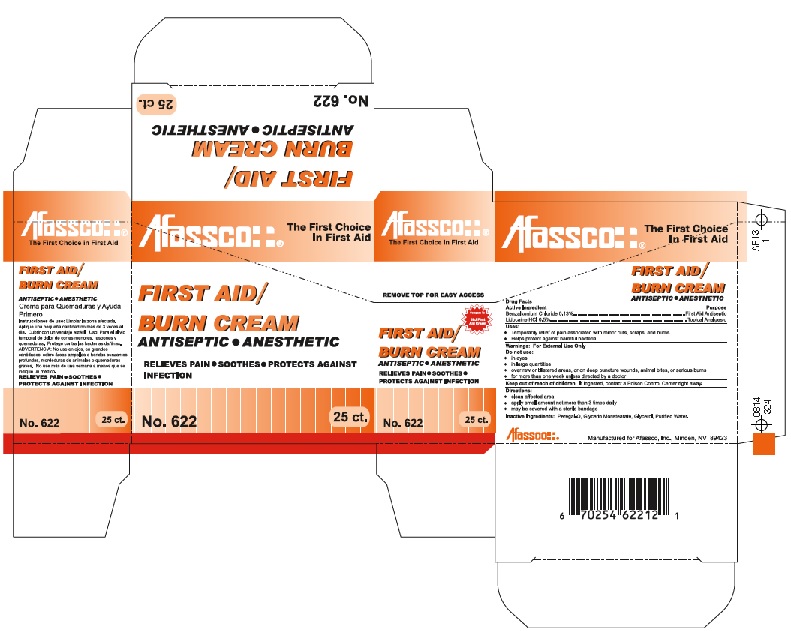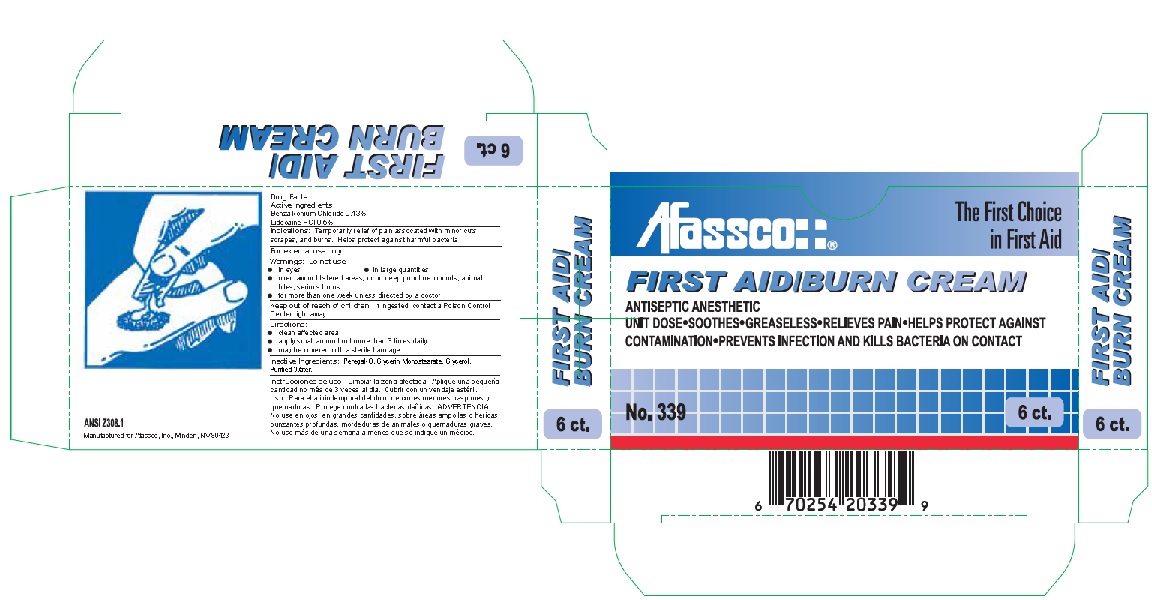 DRUG LABEL: Afassco First Aid Burn Cream
NDC: 51532-4622 | Form: OINTMENT
Manufacturer: Afassco Inc.
Category: otc | Type: HUMAN OTC DRUG LABEL
Date: 20190109

ACTIVE INGREDIENTS: LIDOCAINE HYDROCHLORIDE 0.005 g/1 g; BENZALKONIUM CHLORIDE 0.0013 g/1 g
INACTIVE INGREDIENTS: POLYOXYL 20 CETOSTEARYL ETHER; DIGLYCERIN MONOSTEARATE; GLYCERIN; WATER

Afassco First Aid Burn Cream

Drug Facts

Active Ingredient

Benzalkonium Chloride 0.13%
Lidocaine HCL 0.5%

Purpose First aid antiseptic., external amalgesic

Uses

first aid to help prevent
infection and for the
temporary relief of pain and
itching associated with minor
cuts, scrapes, burns

Warnings

For external use only

Do not use ■ in eyes ■ in

large quantities, over raw

blistered areas, on deep

puncture wounds, animal

bites or serious burns ■ for

more than one wek

Keep out of reach of children

If ingested, contact a Poison

Control Center right away.

Directions

■ clean affected area ■ apply

a small amount on area, not

more than 3 times daily

■ may cover with a sterile bandage

Other Information

store at room temperature

Inactive Ingredients

Peregal-O 2.5%, Glycerin

Monostearate 2.5%, Glycerol

5%, Purified Water

↓Principal Display 6 ct. Package↓

Afassco¦ ¦®

The First Choice

in First Aid

FIRST AID/BURN CREAM

No.339 6 ct.

6 ct.

FIRST AID/
BURN CREAM

ANSI Z308.1

Manufactured for Afassco, Inc., Minden, NV 89423

6 70254 20339 9

↓Principal Display 25 ct. Package↓

↓1 gm Packet↓

res